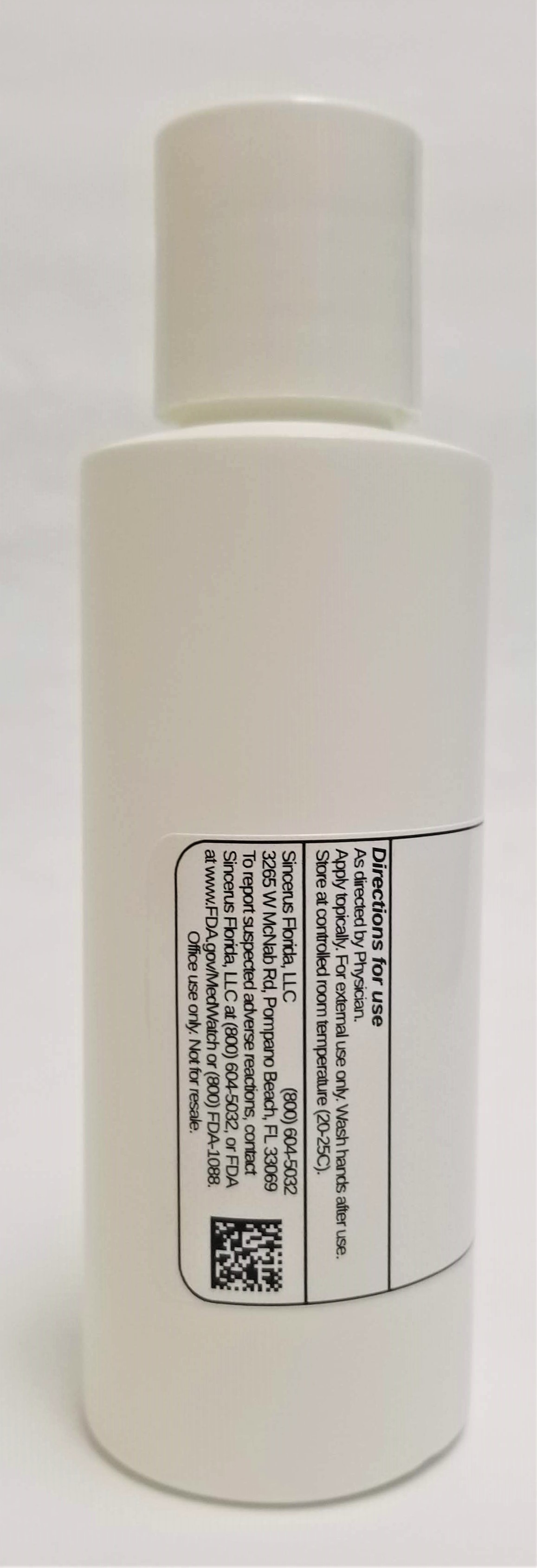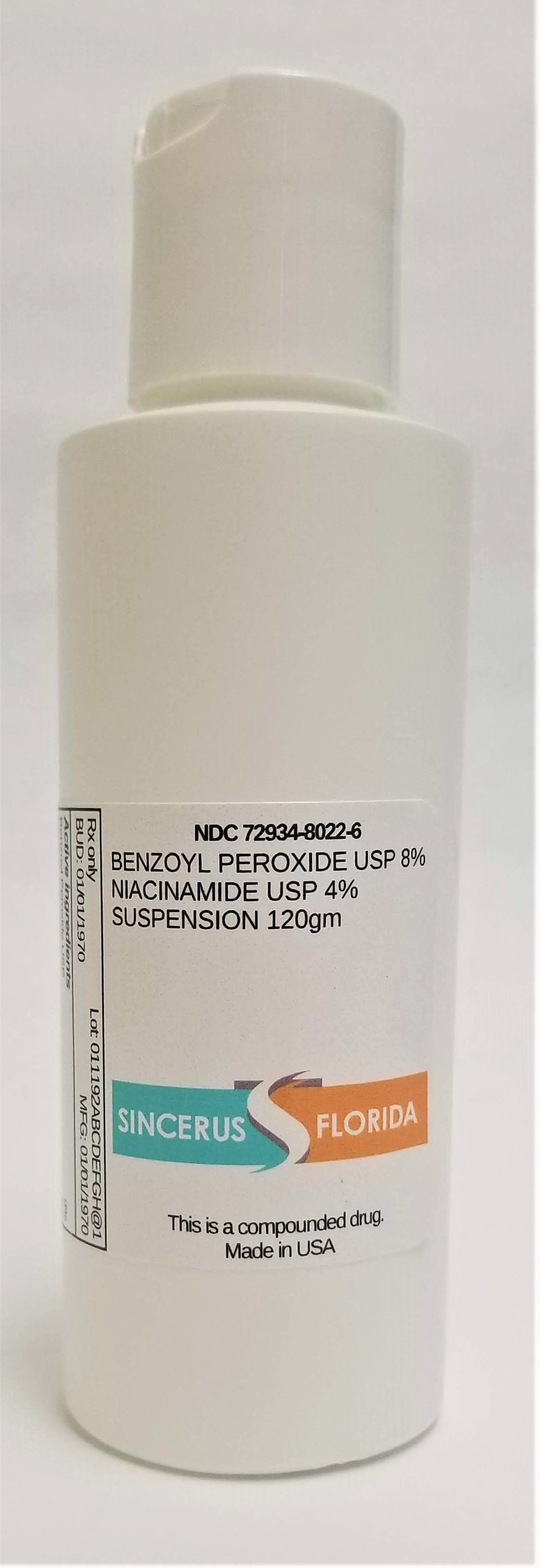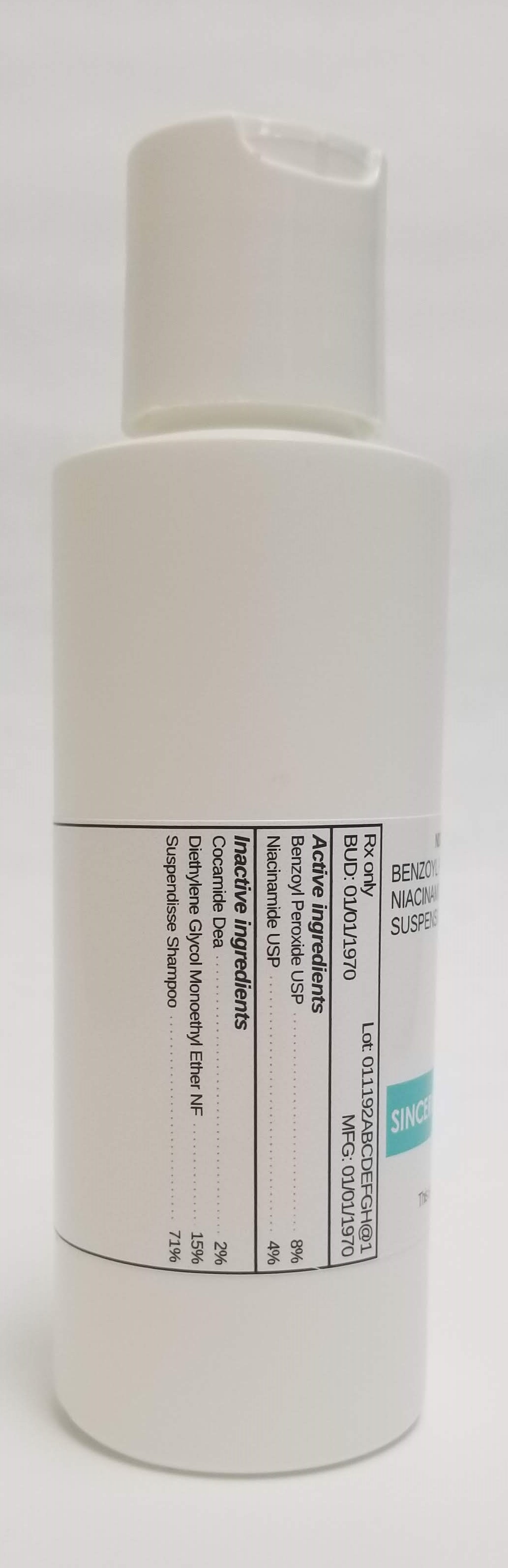 DRUG LABEL: BENZOYL PEROXIDE 8% / NIACINAMIDE 4%
NDC: 72934-8022 | Form: SUSPENSION
Manufacturer: Sincerus Florida
Category: prescription | Type: HUMAN PRESCRIPTION DRUG LABEL
Date: 20190510

ACTIVE INGREDIENTS: BENZOYL PEROXIDE 8 g/100 g; NIACINAMIDE 4 g/100 g

BENZOYL PEROXIDE 8% / NIACINAMIDE 4%